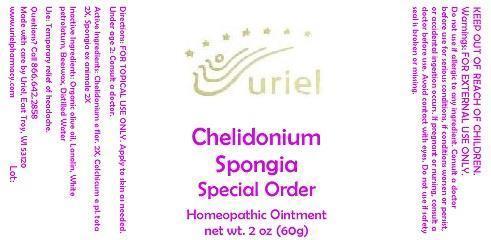 DRUG LABEL: Chelidonium Spongia Special Order
NDC: 48951-3081 | Form: OINTMENT
Manufacturer: Uriel Pharmacy Inc.
Category: homeopathic | Type: HUMAN OTC DRUG LABEL
Date: 20140930

ACTIVE INGREDIENTS: CHELIDONIUM MAJUS 2 [hp_X]/1 g; COLCHICUM AUTUMNALE WHOLE 2 [hp_X]/1 g; SPONGIA OFFICINALIS WHOLE 2 [hp_X]/1 g
INACTIVE INGREDIENTS: OLIVE OIL; LANOLIN; PETROLATUM; YELLOW WAX; WATER

Chelidonium Spongia Special Order

INDICATIONS AND USAGE

Directions: FOR TOPICAL USE ONLY.

DOSAGE AND ADMINISTRATION

Apply to skin as needed. Under age 2: Consult a doctor.

ACTIVE INGREDIENT

Active Ingredients: Chelidonium e flor. 2X, Colchicum e pl. tota 2X, Spongia ex animale 2X

INACTIVE INGREDIENT

Inactive Ingredients: Organic olive oil, Lanolin, White petrolatum, Beeswax, Distilled Water

PURPOSE

Use: Temporary relief of headache.

KEEP OUT OF REACH OF CHILDREN.

WARNINGS

Warnings: FOR EXTERNAL USE ONLY. Do not use if allergic to any ingredient. Consult a doctor before use for serious conditions, if conditions worsen or persist, or accidental ingestion occurs. If pregnant or nursing, consult a doctor before use. Avoid contact with eyes. Do not use if safety seal is broken or missing.

QUESTIONS

Questions? Call 866.642.2858 Made with care by Uriel, East Troy, WI 53120 www.urielpharmacy.com